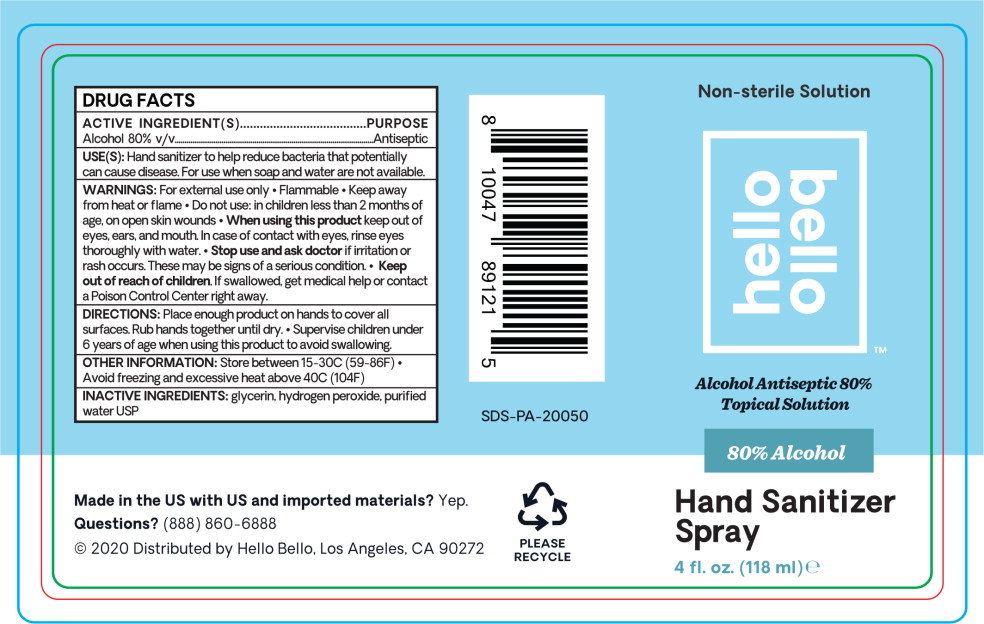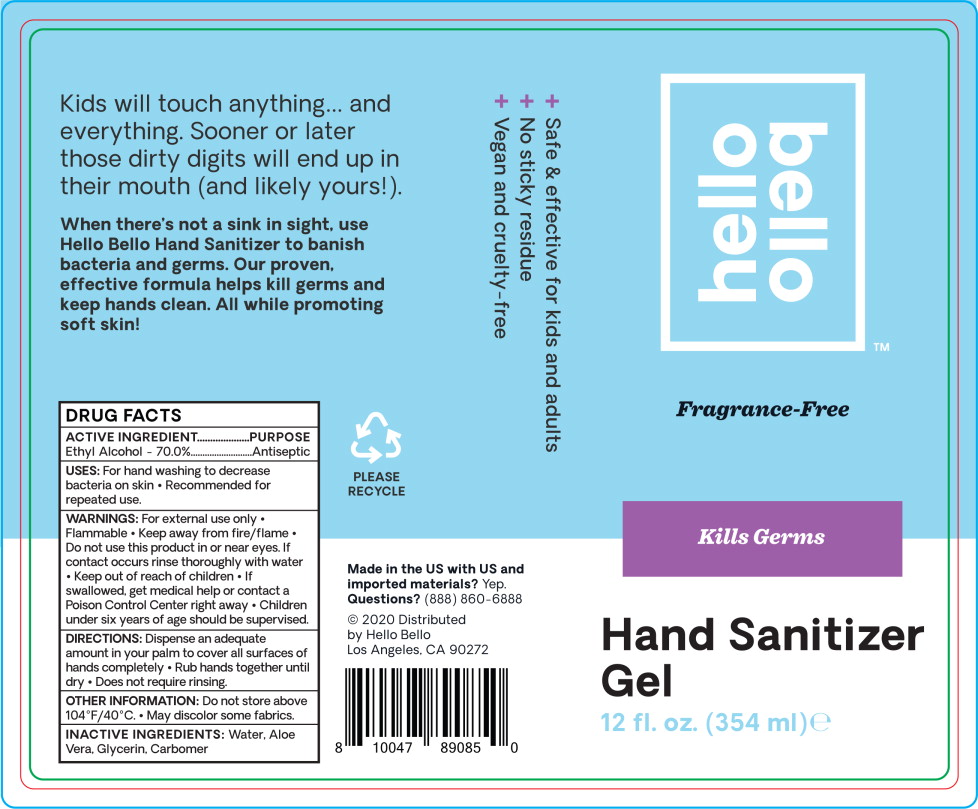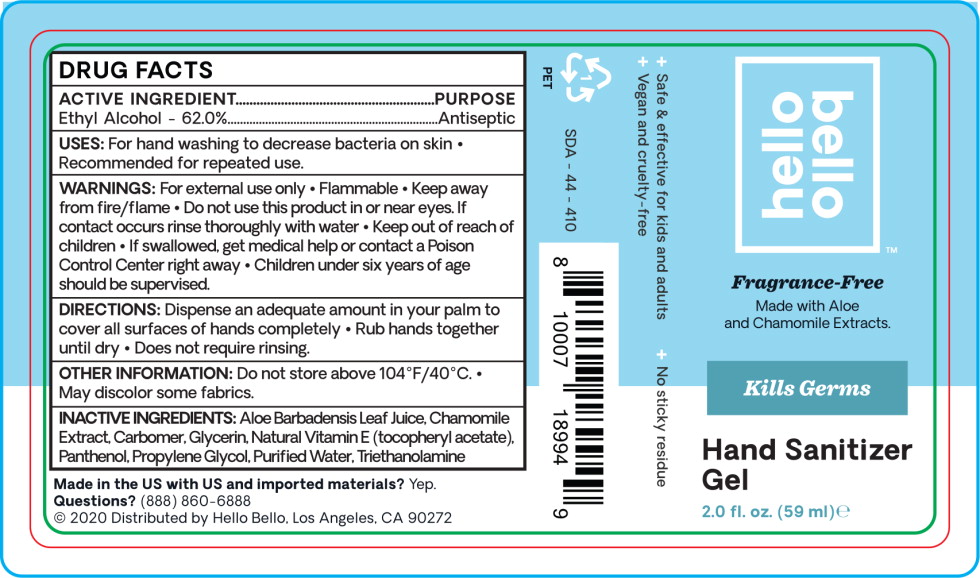 DRUG LABEL: Alcohol
NDC: 73418-039 | Form: SPRAY
Manufacturer: Hello Bello
Category: otc | Type: HUMAN OTC DRUG LABEL
Date: 20210209

ACTIVE INGREDIENTS: Alcohol 80 mL/100 mL
INACTIVE INGREDIENTS: Glycerin; Hydrogen Peroxide; Water

DRUG FACTS

ACTIVE INGREDIENT

Ethyl Alcohol - 62.0%

PURPOSE

Antiseptic

USES:

For hand washing to decrease bacteria on skin

- Recommended for repeated use.

WARNINGS:

For external use only

- Flammable
- Keep away from fire/flame

- Do not use this product in or near eyes. If contact occurs rinse thoroughly with water

- Keep out of reach of children
- If swallowed, get medical help or contact a Poison Control Center right away
- Children under six years of age should be supervised.

DIRECTIONS:

Dispense an adequate amount in your palm to cover all surfaces of hands completely

- Rub hands together until dry
- Does not require rinsing.

OTHER INFORMATION:

Do not store above 104°F/40°C.

- May discolor some fabrics.

INACTIVE INGREDIENTS:

Aloe Barbadensis Leaf Juice. Chamomile Extract Carbomer, Glycerin, Natural Vitamin E (tocopheryl acetate), Panthenol, Propylene Glycol, Purified Water, Triethanolamine

Principal Display Panel – 118 mL Bottle Label

Non-sterile Solution

hello
bello™

Alcohol Antiseptic 80%
Topical Solution

80% Alcohol

Hand Sanitizer
Spray

4 fl. oz. (118 ml) e

Principal Display Panel – 354 mL Bottle Label

hello
bello™

Fragrance-Free

Kills Germs

Hand Sanitizer
Gel

12 fl. oz. (354 ml) e

Principal Display Panel – 59 mL Bottle Label

hello
bello™

Fragrance-Free

Made with Aloe
and Chamomile Extracts.

Kills Germs

Hand Sanitizer
Gel

2.0 fl. oz. (59 ml) e